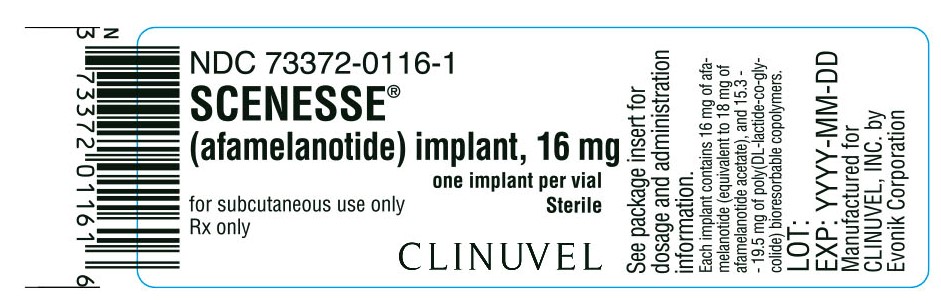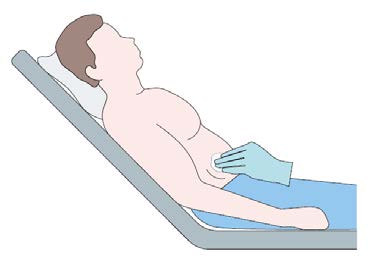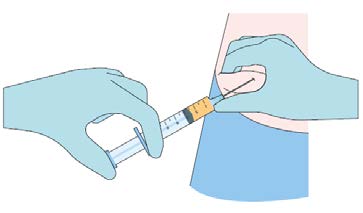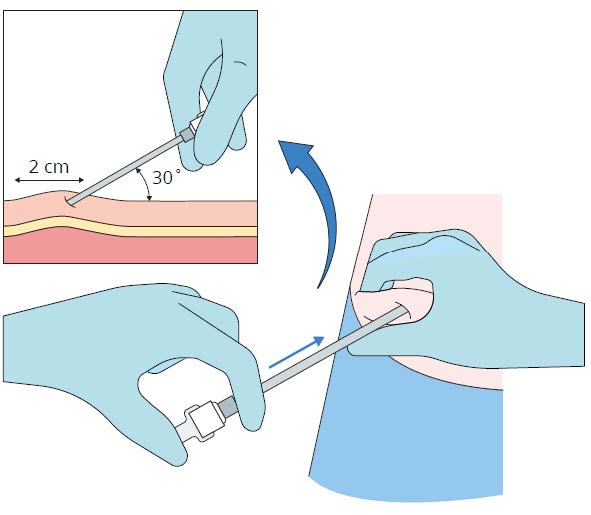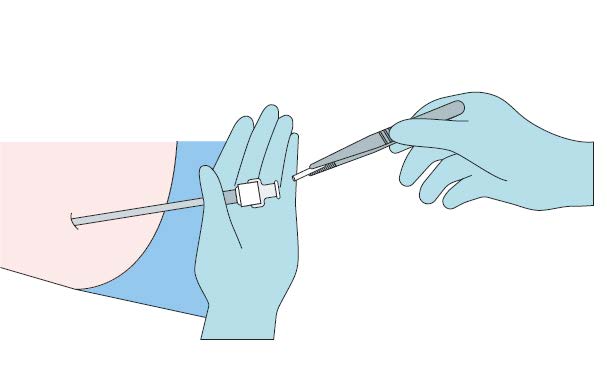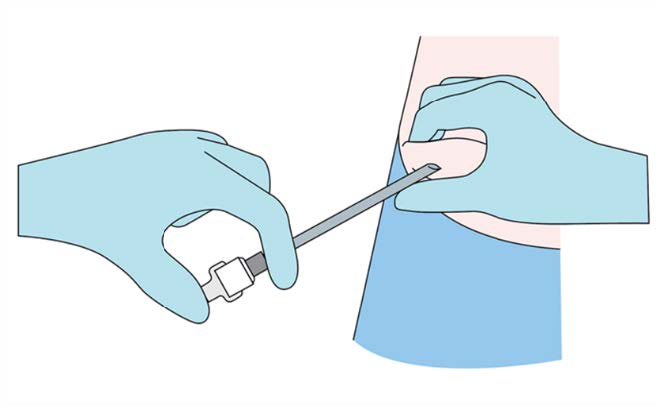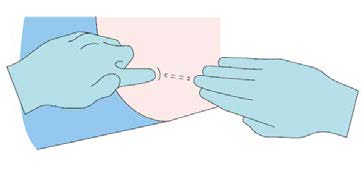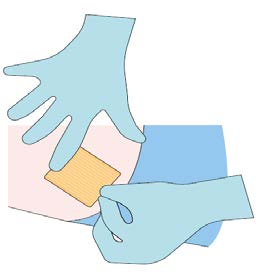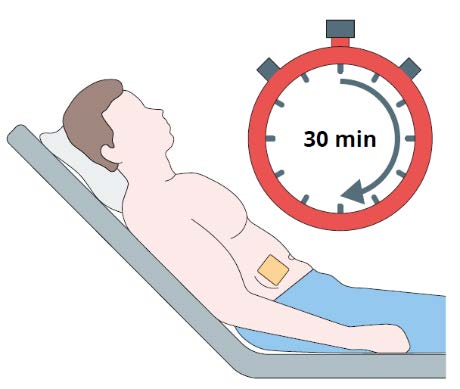 DRUG LABEL: SCENESSE
NDC: 73372-0116 | Form: IMPLANT
Manufacturer: CLINUVEL INC.
Category: prescription | Type: HUMAN PRESCRIPTION DRUG LABEL
Date: 20260202

ACTIVE INGREDIENTS: AFAMELANOTIDE 16 mg/16 mg

HIGHLIGHTS OF PRESCRIBING INFORMATION
These highlights do not include all the information needed to use SCENESSE safely and effectively. See full prescribing information for SCENESSE.
SCENESSE® (afamelanotide) implant, for subcutaneous use.
Initial U.S. Approval: 2019

INDICATIONS AND USAGE

SCENESSE is a melanocortin 1 receptor (MC1-R) agonist indicated to increase pain free light exposure in adult patients with a history of phototoxic reactions from erythropoietic protoporphyria (EPP)

Important Dosage and Administration Information

- SCENESSE should be administered by a healthcare professional who is proficient in the subcutaneous implantation procedure and has completed training prior to administration.
- Insert a single implant, containing 16 mg of afamelanotide, using an Cannula.
- Administer SCENESSE subcutaneously every 2 months.
- See Full Prescribing Information for instructions for removal of SCENESSE.

DOSAGE FORMS AND STRENGTHS

Implant: 16 mg of afamelanotide.

CONTRAINDICATIONS

Known hypersensitivity to afamelanotide or to any of the excipients in SCENESSE.

Hypersensitivity Skin Monitoring

Hypersensitivity: Serious hypersensitivity reactions, including anaphylaxis, have been reported. If a serious hypersensitivity reaction occurs, initiate appropriate therapy and remove the SCENESSE implant if needed. The patient should not receive any further treatment with SCENESSE.

Skin Monitoring: May induce darkening of pre-existing nevi and ephelides due to its pharmacological effect. A full body skin examination (twice yearly) is recommended to monitor pre-existing nevi and new skin pigmentary lesions.

Clinical Trials Experience

The most common adverse reactions (incidence > 2%) are implant site reaction, nausea, oropharyngeal pain, cough, fatigue, dizziness, skin hyperpigmentation, somnolence, melanocytic nevus, respiratory tract infection, non-acute porphyria, and skin irritation.
To report SUSPECTED ADVERSE REACTIONS, contact CLINUVEL INC. at 1-888-288-2031 or FDA at 1-800-FDA-1088 or www.fda.gov/medwatch.
See PATIENT COUNSELING INFORMATION.

RECENT MAJOR CHANGES

Dosage and Administration08/2024
Contraindications08/2024
Warnings and Precautions08/2024

FULL PRESCRIBING INFORMATION

INDICATIONS AND USAGE

SCENESSE®is indicated to increase pain free light exposure in adult patients with a history of phototoxic reactions from erythropoietic protoporphyria (EPP).

Important Dosage and Administration Information

SCENESSE should be administered by a health care professional. All healthcare professionals should be proficient in the subcutaneous implantation procedure and have completed the training program provided by CLINUVEL prior to administration of the SCENESSE implant [ see Dosage and Administration]. Additional information, including a video, is available at http://www.clinuvel.com/US-HCP. The additional information has not been evaluated or approved by the FDA.

Insert a single SCENESSE implant subcutaneously above the anterior supra-iliac crest every 2 months.

Use the SFM Implantation Cannula to implant SCENESSE.

Maintain sun and light protection measures during treatment with SCENESSE to prevent phototoxic reactions related to EPP.

Instructions for Implantation of SCENESSE

Insert a single SCENESSE implant (containing 16 mg of afamelanotide) subcutaneously above the anterior supra-iliac crest.
Implant SCENESSE observing an aseptic technique. The following equipment is needed for the implant insertion:

- SCENESSE implant
- SFM Implantation Cannula; use of a device that has not been determined to be suitable could result in damage to the SCENESSE implant [ see Dosage and Administration].
- Sterile gloves
- Local anesthetic, needle and syringe
- Blunt forceps suitable for removing the SCENESSE implant from the glass vial and placement of the SCENESSE implant
- Sterile gauze, adhesive bandage, pressure bandage

Step 1

- Take the carton containing SCENESSE out of the refrigerator to allow the product to gradually warm up to ambient temperature.
- Remove the seal and stopper from the glass vial containing SCENESSE. Remove the implant from the vial using the blunt forceps under aseptic conditions and place the implant on a sterile gauze.

Step 2
Put the patient in a comfortable reclined supine position.
Identify the insertion site 3-4 cm above the anterior supra-iliac crest and disinfect the skin surface.

Step 3 (optional)
Anesthetize the area of insertion (puncture) if deemed necessary and in consultation with the patient.

Step 4
While pinching the skin of the insertion site, insert the cannula with the bevel facing upwards (away from the abdomen) at a 30-45° angle into the subcutaneous layer.
Advance the cannula 2 cm into the subcutaneous layer.

Step 5

- Remove the stylet (obturator) from the cannula maintaining aseptic precautions.
- Load the implant into the cannula.
- Using the stylet (obturator) gently push the implant down the full length of the cannula’s shaft.

Step 6
Apply pressure to the site of the implant while removing the stylet (obturator) and the cannula. Verify that no implant or
implant portion remains in the cannula.

Step 7
Verify the correct insertion and placement of the implant by palpating the skin overlying the implant.

Step 8
Apply dressing to the insertion site. Leave dressing in place for 24 hours.

Step 9
Monitor the patient for 30 minutes after the implant administration.

Instructions for Removal of SCENESSE

In case a clinical necessity arises to remove the implant, follow the procedure described below:
• palpate the area of implant insertion
• locate the position of the implant (*Note that the implant is resorbable and may not be able to be located from 10 days after insertion)
• inject local anesthetic at the site of foreseen puncture
• wait for the local anesthetic to take effect
• puncture the dermis at the site of previous insertion
• digitally locate the trajectory of the implant
• put digital pressure on the dermis– at the distal end of the implant
• remove the implant by digitally pushing the implant out towards the puncture site (aperture)
• use a pressure compress or band aid on the aperture
• observe the patient for 15 minutes after removal of the implant
• instruct the patient to maintain the pressure compress for 12 hours.
*Note: The implant may not be palpable due to resorption, and removal would likely not be possible. In the unlikely event of the need to surgically remove SCENESSE, it may be localized by ultrasound.

DOSAGE FORMS AND STRENGTHS

Implant: 16 mg of afamelanotide as a solid white to off-white, bioresorbable, sterile rod approximately 1.7 cm in length and 1.45 mm in diameter.

CONTRAINDICATIONS

SCENESSE is contraindicated in patients with a history of severe hypersensitivity reaction to afamelanotide or to any of the excipients in SCENESSE.

Hypersensitivity Skin Monitoring

Serious hypersensitivity reactions, including anaphylaxis, have been reported with postmarket use of SCENESSE. Warn patients of the risk of hypersensitivity reactions, including anaphylaxis. If a serious hypersensitivity reaction occurs, initiate appropriate therapy and remove the SCENESSE implant if needed [ see Dosage and Administration]. The patient should not receive any further treatment with SCENESSE. [ see Contraindications].

SCENESSE may lead to generalized increased skin pigmentation and darkening of pre-existing nevi and ephelides because of its pharmacologic effect. A full body skin examination (twice yearly) is recommended to monitor pre-existing and new skin pigmentary lesions.

Clinical Trials Experience

Because clinical trials are conducted under widely varying conditions, adverse reaction rates observed in the clinical trials of a drug cannot be directly compared to rates in the clinical trials of another drug and may not reflect the rates observed in practice.

The safety of SCENESSE was evaluated in 3 randomized, multicenter, prospective, vehicle controlled clinical trials (Study CUV029, Study CUV030, and Study CUV039) involving 244 adult subjects with erythropoietic protoporphyria (EPP) without significant liver involvement. Subjects received subcutaneous SCENESSE implants containing 16 mg of afamelanotide every 2 months. A total of 125 subjects received SCENESSE and 119 subjects received vehicle implants.

Table 1 summarizes the adverse reactions that occurred in more than 2% of subjects.

Table 1: Adverse Reactions Occurring in More Than 2% of Subjects with EPP Through Month 6 (Studies CUV039, CUV030, and CUV029).

Table 1: Adverse Reactions Occurring in More Than 2% of Subjects with EPP Through Month 6 (Studies CUV039, CUV030, and CUV029)
Adverse Reaction | SCENESSE n (%) N = 125 | Vehicle n (%) N = 119
Implant site reaction^1 | 26 (21%) | 12 (10%)
Nausea | 24 (19%) | 17 (14%)
Oropharyngeal pain | 9 (7%) | 6 (5%)
Cough | 8 (6%) | 4 (3%)
Fatigue | 7 (6%) | 3 (3%)
Skin hyperpigmentation^2 | 5 (4%) | 0 (0%)
Dizziness | 5 (4%) | 4 (3%)
Melanocytic nevus | 5 (4%) | 2 (2%)
Respiratory tract infection | 5 (4%) | 3 (3%)
Somnolence | 3 (2%) | 1 (1%)
Non-acute porphyria | 2 (2%) | 0 (0%)
Skin irritation | 2 (2%) | 0 (0%)

^1: Implant site reaction includes: implant site bruising, discoloration, erythema, hemorrhage, hypertrophy, irritation, nodule, pain, pruritus, swelling;
injection site bruising and erythema; and expelled implant.
^2: Skin hyperpigmentation includes skin hyperpigmentation, pigmentation lip (subject also had skin hyperpigmentation), and pigmentation disorder.

Specific Adverse Reactions
Implant Site Reactions: Implant site reactions were more common in the SCENESSE group (21%) compared to the vehicle
group (10%). In the SCENESSE group, the most common implant site reaction was implant site discoloration (10%).

Postmarketing Experience

The following adverse reactions have been identified during post-approval use of SCENESSE. Because these reactions are reported voluntarily from a population of uncertain size, it is not always possible to reliably estimate their frequency or establish a causal relationship to drug exposure.
Immune System Disorders: hypersensitivity (urticaria, angioedema, and anaphylaxis) [ see Warnings and Precautions].

Pregnancy

Risk Summary
There are no data on SCENESSE use in pregnant women to evaluate for any drug associated risk of major birth defects, miscarriage, or adverse maternal or fetal outcome.

In animal reproductive and development toxicity studies, no adverse developmental effects were observed with afamelanotide administration during the period of organogenesis to pregnant rats at subcutaneous doses up to 12 times the maximum recommended human dose (MRHD) (see Data).

All pregnancies have a background risk of birth defect, loss, or other adverse outcomes. The estimated background risk of major birth defects and miscarriage for the indicated population is unknown. In the U.S. general population, the estimated background risk of major birth defects and miscarriage in clinically recognized pregnancies is 2% to 4% and 15% to 20%, respectively.

Data
Animal Data
In embryofetal development studies in Sprague Dawley and Lister Hooded rats, afamelanotide was administered subcutaneously to pregnant rats at doses of 0.2, 2, or 20 mg/kg/day throughout the period of organogenesis. No adverse embryofetal developmental effects were observed at doses up to 20 mg/kg/day (12 times the MRHD, based on a body surface area comparison).

In a pre- and post-natal development study in Sprague Dawley rats, afamelanotide was administered subcutaneously at doses of 0.2, 2, or 20 mg/kg/day during the period of organogenesis through lactation. No treatment-related effects were observed at doses up to 20 mg/kg/day (12 times the MRHD, based on a body surface area comparison).

Lactation

Risk Summary
There are no data on the presence of afamelanotide or any of its metabolites in human or animal milk, the effects on the breastfed infant, or the effect on milk production. The developmental and health benefits of breastfeeding should be considered along with the mother’s clinical need for SCENESSE and any potential adverse effects on the breastfed infant from SCENESSE or from the underlying maternal condition.

Pediatric Use

The safety and effectiveness of SCENESSE have not been established in pediatric patients.

Geriatric Use

There were 10 subjects 65 years old and over in the clinical studies for EPP [ see Clinical Studies]. Of the 125 subjects treated with SCENESSE in these studies, 4 (3%) were 65 years of age and older. Clinical studies of SCENESSE did not include sufficient numbers of subjects aged 65 and over to determine whether they respond differently from younger subjects. Other reported clinical experience has not identified differences in responses between the elderly and younger patients.

Descripton

SCENESSE (afamelanotide) implant is a controlled-release dosage form for subcutaneous administration. Afamelanotide is a melanocortin 1 receptor (MC1-R) agonist. The active ingredient afamelanotide acetate is a synthetic peptide containing 13 amino acids with molecular formula C78H111N21O19•xC2H4O2(3 ≤ x ≤ 4). The molecular weight of afamelanotide is 1646.85 (anhydrous free base). Afamelanotide acetate has the following structure:

Ac-Ser-Tyr-Ser-Nle-Glu-His-(D)Phe-Arg-Trp-Gly-Lys-Pro-Val-NH2• xCH3COOH.

Afamelanotide is a white to off-white powder, freely soluble in water. Each SCENESSE implant contains 16 mg of afamelanotide (equivalent to 18 mg of afamelanotide acetate), and 15.3-19.5 mg of poly (DL-lactide-co-glycolide).
SCENESSE implant is a single, solid white to off-white, bioresorbable and sterile rod approximately 1.7 cm in length and 1.45 mm in diameter. The implant core comprises of the drug substance admixed with a poly (DL-lactide-co-glycolide) bioresorbable copolymer.

Mechanism of Action

Afamelanotide is a synthetic tridecapeptide and a structural analog of α-melanocyte stimulating hormone (α-MSH).
Afamelanotide is a melanocortin receptor agonist and binds predominantly to MC1-R.

Pharmacodynamics

Afamelanotide increases production of eumelanin in the skin independently of exposure to sunlight or artificial UV light sources.

Pharmacokinetics

The pharmacokinetics of afamelanotide following administration of a single subcutaneous implant of SCENESSE were evaluated in 12 healthy adults. High variability was observed in the plasma concentrations of afamelanotide and for most subjects (9 out of 12), the last measurable afamelanotide concentration was at 96 hours post-dose. The mean ± SD Cmaxand AUC0-infwere 3.7 ± 1.3 ng/mL and 138.9 ± 42.6 hr*ng/mL, respectively.

Absorption

The median Tmaxwas 36 hr.

Elimination

The apparent half-life of afamelanotide is approximately 15 hr when administered subcutaneously in a controlled release
implant.

Metabolism

Afamelanotide may undergo hydrolysis. However, its metabolic profile has not been fully characterized.

Specific Populations

The effect of renal or hepatic impairment on the pharmacokinetics of afamelanotide is unknown.

Drug Interaction Studies

No drug interaction studies were conducted with afamelanotide.

Carcinogenesis, Mutagenesis, Impairment of Fertility

Carcinogenicity studies have not been conducted with SCENESSE.

Afamelanotide was negative in the Ames test, in vitromouse lymphoma assay, and in vivomouse bone marrow micronucleus assay.

No effects on male or female fertility and reproductive performance were observed in rats at subcutaneous doses up to 20 mg/kg/day afamelanotide (12 times the MRHD, based on a body surface area comparison).

CLINICAL STUDIES

Three vehicle-controlled, parallel-group clinical trials of SCENESSE were conducted in subjects with EPP. Of these trials, two trials (Study CUV039, NCT 01605136, and Study CUV029, NCT 00979745) were designed to assess exposure to direct sunlight on days with no phototoxic pain. The two trials differed in the number of days of follow-up, the time windows within a day in which time spent outdoors was recorded, and how the amount of time spent in direct sunlight on each day was characterized. The subjects enrolled in these trials were primarily Caucasian (98%), the mean age was 40 years (range 18 to 74 years), and 53% of subjects were male and 47% were female.

Study CUV039 enrolled 93 subjects, of whom 48 received SCENESSE (16 mg of afamelanotide administered subcutaneously every 2 months), 45 received vehicle. Subjects received three implants and were followed for 180 days. On each study day, subjects recorded the number of hours spent in direct sunlight between 10 am and 6 pm, the number of hours spent in shade between 10 am and 6 pm, and whether they experienced any phototoxic pain that day. The primary endpoint was the total number of hours over 180 days spent in direct sunlight between 10 am and 6 pm on days with no pain. The median total number of hours over 180 days spent in direct sunlight between 10 am and 6 pm on days with no pain was 64.1 hours for subjects receiving SCENESSE and 40.5 hours for subjects receiving vehicle.

Study CUV029 enrolled 74 subjects, of whom 38 received SCENESSE (16 mg of afamelanotide administered subcutaneously every 2 months), 36 received vehicle. Subjects received five implants and were followed for 270 days. On each study day, subjects recorded the number of hours spent outdoors between 10 am and 3 pm, whether “most of the day” was spent in direct sunlight, shade, or a combination of both, and whether they experienced any phototoxic pain that day.
The primary endpoint was the total number of hours over 270 days spent outdoors between 10 am and 3 pm on days with no pain for which “most of the day” was spent in direct sunlight. This analysis does not include sun exposure on days for which subjects reported spending time in a combination of both direct sunlight and shade. The median total number of hours over 270 days spent outdoors between 10 am and 3 pm on days with no pain for which “most of the day” was spent in direct sunlight was 6.0 hours for subjects in the SCENESSE group and 0.75 hours for subjects in the vehicle group.

HOW SUPPLIED

SCENESSE (afamelanotide) implant, 16 mg, for subcutaneous administration (NDC 73372-0116-1) is supplied in a Type I amber glass vial sealed with a PTFE coated rubber stopper. Each vial contains one afamelanotide implant and is packaged individually in a cardboard box. SCENESSE implant is a solid white to off-white, bioresorbable and sterile rod approximately 1.7 cm in length and 1.45 mm in diameter.

STORAGE AND HANDLING

Store in a refrigerator at 2°C – 8°C (36°F-46°F). Protect from light.
SCENESSE implants are not supplied with an implantation device for subcutaneous administration [ see Dosage and Administration].

PATIENT COUNSELING INFORMATION

Hypersensitivity Reactions
Advise patients who experience any symptoms of serious hypersensitivity reactions to seek immediate medical attention for treatment and possible removal of the SCENESSE implant [see Warnings and Precautions].

Concomitant Measures

Advise patients to maintain sun and light protection measures during treatment with SCENESSE to prevent phototoxic reactions related to EPP [ see Dosage and Administration].

Skin Monitoring

Advise patients that darkening of pre-existing nevi and ephelides may occur with use of SCENESSE. A full body skin examination is recommended twice yearly to monitor pre-existing and new skin pigmentary lesions [ see Warnings and Precautions].

Expelled Implant
Advise patients to contact their healthcare provider if the implant is expelled.

Dressing removal

Advise patients that the dressing can be removed after 24 hours [ see Dosage and Administration].

Insertion Site Care and Monitoring
Advise patients to monitor the insertion site after dressing removal and to report any reaction observed at the site to their healthcare provider.

RECENT MAJOR CHANGES

Dosage and Administration

Instructions for Removal of SCENESSE
In case a clinical necessity arises to remove the implant, follow the procedure described below:
• palpate the area of implant insertion
• locate the position of the implant (*Note that the implant is resorbable and the implant may not be able to be located
from 10 days after insertion).
• inject local anesthetic at the site of foreseen puncture
• wait for the local anesthetic to take effect
• puncture the dermis at the site of previous insertion
• digitally locate the trajectory of the implant
• put digital pressure on the dermis– at the distal end of the implant
• remove the implant by digitally pushing the implant out towards the puncture site (aperture)
• use a pressure compress or band aid on the aperture
• observe the patient for 15 minutes after removal of the implant
• instruct the patient to maintain the pressure compress for 12 hours.
*Note: The implant may not be palpable due to resorption, and removal would likely not be possible. In the unlikely event
of the need to surgically remove SCENESSE, it may be localized by ultrasound.

Contraindications

SCENESSE is contraindicated in patients with a history of severe hypersensitivity reaction to afamelanotide or to any of the excipients in SCENESSE [ see Warnings and Precautions]

Hypersensitivity

Serious hypersensitivity reactions, including anaphylaxis, have been reported with postmarket use of SCENESSE. Warn patients of the risk of hypersensitivity reactions, including anaphylaxis. If a serious hypersensitivity reaction occurs, initiate appropriate therapy and remove the SCENESSE implant if needed [ see Dosage and Administration]. The patient should not receive any further treatment with SCENESSE [ see Contraindications].